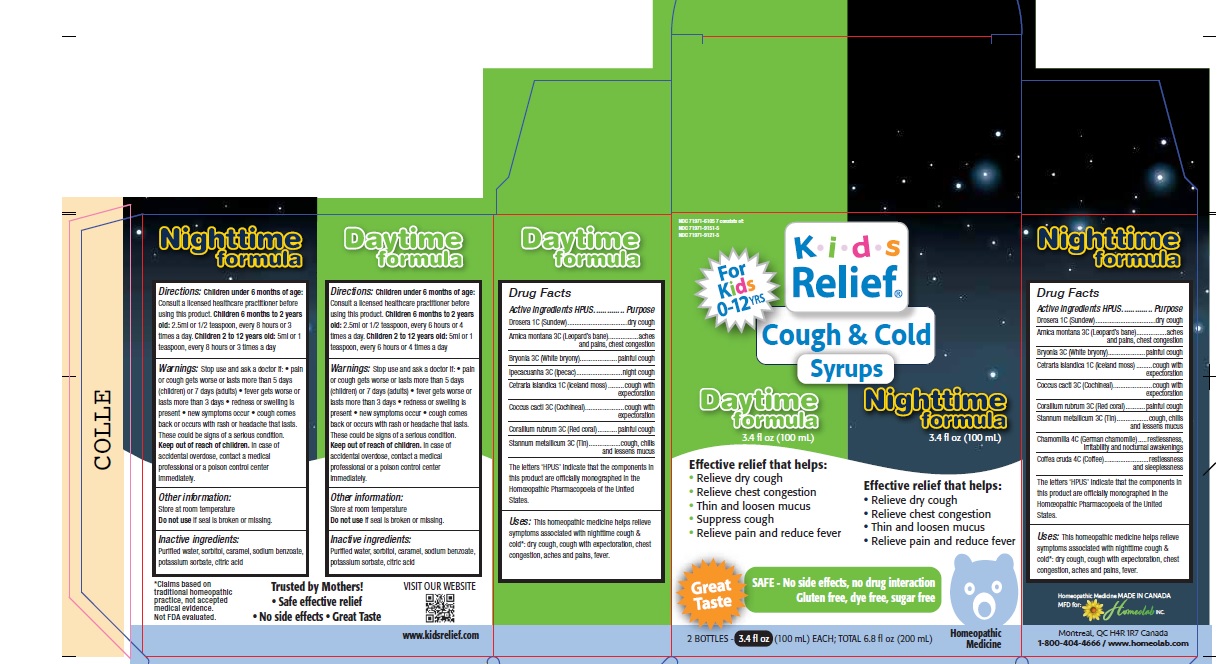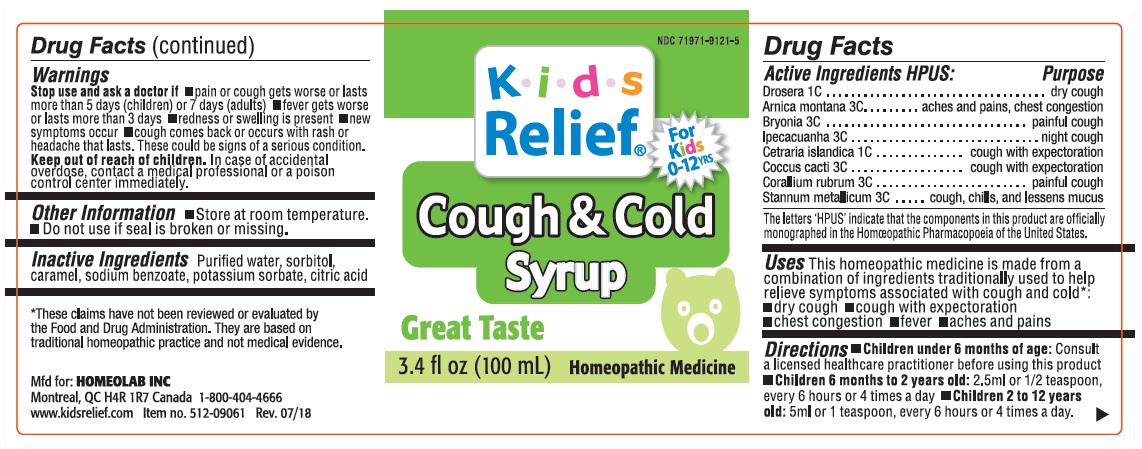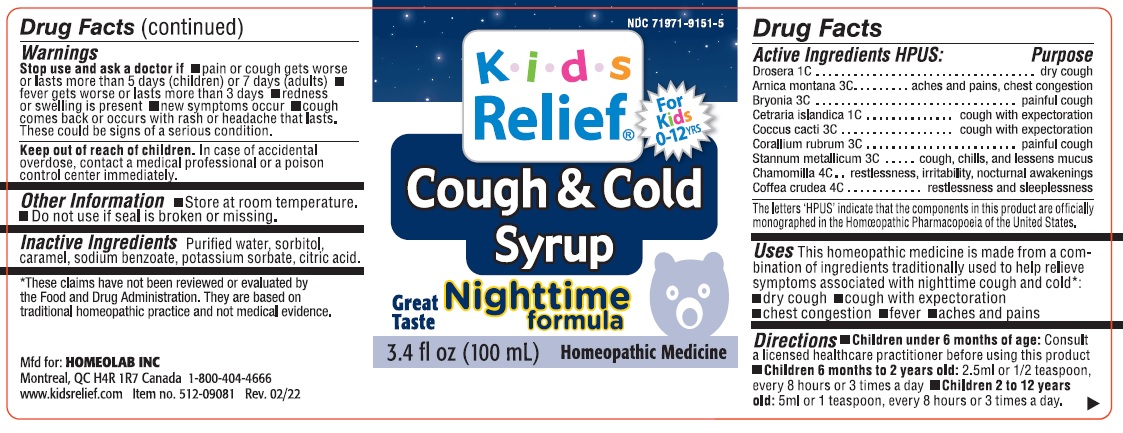 DRUG LABEL: Kids Relief Cough and Cold Syrup Combo Pack Daytime Formula and Nighttime Formula
NDC: 71971-6105 | Form: KIT | Route: ORAL
Manufacturer: Homeolab International (Canada) inc
Category: homeopathic | Type: HUMAN OTC DRUG LABEL
Date: 20250730

ACTIVE INGREDIENTS: DROSERA ROTUNDIFOLIA FLOWERING TOP 1 [hp_C]/100 mL; ARNICA MONTANA 3 [hp_C]/100 mL; BRYONIA ALBA WHOLE 3 [hp_C]/100 mL; IPECAC 3 [hp_C]/100 mL; CETRARIA ISLANDICA WHOLE 1 [hp_C]/100 mL; COCHINEAL 3 [hp_C]/100 mL; CORALLIUM RUBRUM WHOLE 3 [hp_C]/100 mL; TIN 3 [hp_C]/100 mL; DROSERA ROTUNDIFOLIA FLOWERING TOP 1 [hp_C]/100 mL; ARNICA MONTANA 3 [hp_C]/100 mL; BRYONIA ALBA WHOLE 3 [hp_C]/100 mL; CETRARIA ISLANDICA WHOLE 1 [hp_C]/100 mL; PROTORTONIA CACTI 3 [hp_C]/100 mL; TIN 3 [hp_C]/100 mL; CHAMOMILE 4 [hp_C]/100 mL; ARABICA COFFEE BEAN 4 [hp_C]/100 mL; CORALLIUM RUBRUM WHOLE 3 [hp_C]/100 mL
INACTIVE INGREDIENTS: WATER; CARAMEL; SORBITOL; SODIUM BENZOATE; POTASSIUM SORBATE; CITRIC ACID MONOHYDRATE; WATER; SORBITOL; CARAMEL; SODIUM BENZOATE; POTASSIUM SORBATE; CITRIC ACID MONOHYDRATE

Active Ingredients

Part 1 -Cough Cold Daytime Syrup

DROSERA ROTUNDIFOLIA FLOWERING TOP
ARNICA MONTANA
BRYONIA ALBA WHOLE
IPECACUANHA (IPECAC)
CETRARIA ISLANDICA SUBSP. ISLANDICA
COCHINEAL (COCCUS CACTI)
CORALLIUM RUBRUM WHOLE
STANNUM METALLICUM (TIN)

Part 2 -Cough Cold Nighttime Syrup

DROSERA ROTUNDIFOLIA FLOWERING TOP
ARNICA MONTANA
BRYONIA ALBA WHOLE
CETRARIA ISLANDICA SUBSP. ISLANDICA
COCHINEAL (COCCUS CACTI)
CORALLIUM RUBRUM WHOLE
STANNUM METALLICUM (TIN)
CHAMOMILLA (GERMAN CHAMOMILLE)
COFFEA CRUDA (COFFEE)

Purpose

Part 1 - Cough Cold Daytime Syrup

DROSERA ROTUNDIFOLIA FLOWERING TOP Dry Cough
ARNICA MONTANA Aches and Pain , Chest Congestion
BRYONIA ALBA WHOLE Painful Cough
IPECACUANHA (IPECAC) Night Cough
CETRARIA ISLANDICA SUBSP. ISLANDICA Cough With Expectoration
COCHINEAL (COCCUS CACTI) Cough With Expectoration
CORALLIUM RUBRUM WHOLE Painful cough
STANNUM METALLICUM (TIN) Cough, Chills and Lessen mucus

Part 2 - Cough Cold Nighttime Syrup

DROSERA ROTUNDIFOLIA FLOWERING TOP Dry Cough
ARNICA MONTANA Aches and Pain , Chest Congestion
BRYONIA ALBA WHOLE Painful Cough
CETRARIA ISLANDICA SUBSP. ISLANDICA Cough With Expectoration
COCHINEAL (COCCUS CACTI) Cough With Expectoration
CORALLIUM RUBRUM WHOLE Painful cough
STANNUM METALLICUM (TIN) Cough, Chills and Lessen mucus
CHAMOMILLA (GERMAN CHAMOMILLE) Restlessness, irritability and nocturnal awakening
COFFEA CRUDA (COFFEE) Restlessness and sleeplessness

The letters 'HPUS' indicate that the components in this product are officially monographed in the Homoeopathic Pharmacopoeia of the United States.

Uses

T his ho meo pathic medicine is made from a combination of ingredients traditionally used to help symptoms associated with nighttime cough and cold*; dry cough, cough with expectorantion, chest congestion, aches and pain,fever.

*Claims based on traditional homeopathic practice, not accepted medical evidence. Not FDA evaluated.

Warnings

Stop use and ask a doctor if: • Pain & cough get worse or last more than 5 days (children) or 7 days (adults). • Fever gets worse or lasts more than 3 days. • Redness or swelling is present. • New symptoms occur. • cough comes back or occurs with rash or headache that lasts. These could be signs of a serious condition.

Keep out of reach of children. In case of accidental overdose, contact a medical

professional or poison control center immediately.

Directions

Part 1 Kids Relief Daytime Syrup

Children under 6 months of age: consult a licensed healthcare practitioner before using the product. Children 6 months to 2 years old: 2.5 ml or ½ teaspoon, every 6 hours or 4 times a day. Children 2 to 12 years old: 5 ml or 1 teaspoon, every 6 hours or 4 times a day.

Part 2 Kids Relief Nighttime Syrup

Children under 6 months of age: consult a licensed healthcare practitioner before using the product. Children 6 months to 2 years old: 2.5 ml or ½ teaspoon, every 8 hours or 3 times a day. Children 2 to 12 years old: 5 ml or 1 teaspoon, every 8 hours or 3 times a day.

Other information

Part 1

Do not use if the seal is broken or missing. Store at room temperature.

Part 2

Store at room temperature.• Do not use if seal is broken or missing

*These claims have not been reviewed by the Food and Drug Administration. They are based on traditional homeopathic practice, not medical evidence.

Inactive ingredients

Purified water, sorbitol, caramel, sodium benzoate, potassium sorbate, citric acid.